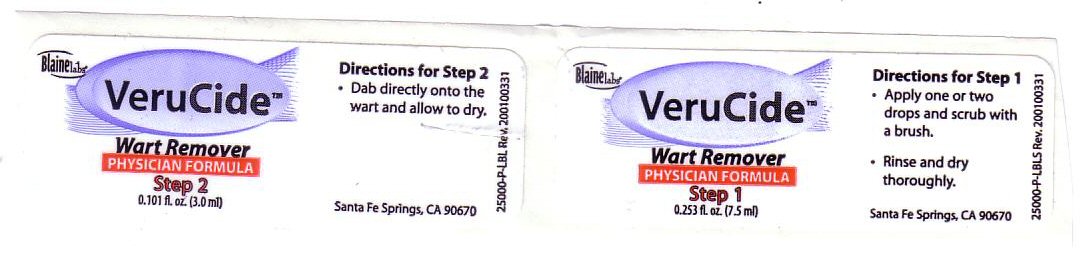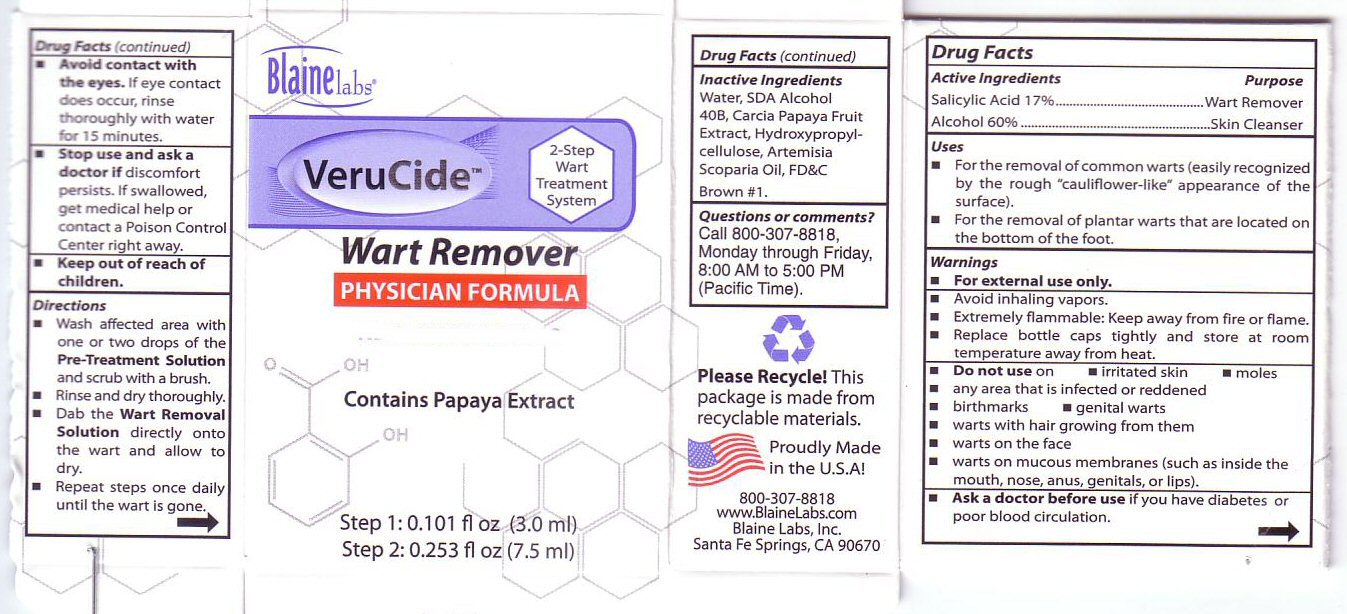 DRUG LABEL: Verucide Physician Formula
NDC: 63347-700 | Form: LIQUID
Manufacturer: Blaine Labs Inc.
Category: otc | Type: HUMAN OTC DRUG LABEL
Date: 20110320

ACTIVE INGREDIENTS: SALICYLIC ACID 17 mL/10 mL
INACTIVE INGREDIENTS: WATER; PAPAYA JUICE; HYDROXYPROPYL CELLULOSE; WORMWOOD OIL; D&C BROWN NO. 1; DENATONIUM BENZOATE; ALCOHOL 60 mL/100 mL

Active Ingredients

Salicylic Acid 17%

Alcohol 60%

Inactive Ingredients

Water, SDA Alcohol 40B, Carcia Papaya Fruit Extract, Hydroxypropyl-cellulose, Artemisia Scoparia Oil, FD C Brown 1

Purpose

Wart Removal

Skin Cleanser

Uses

For the removal of common warts (easily recognized by the rough cauliflower-like appearance of the surface) For the removal of plantar warts that are located on the bottom of the foot.

Directions

Wash Affected area with one or two drops of the Pre-Treatment Solution and scrub with a brush. Rinse and dry thoroughly. Dab the wart removal solution directly onto the wart and allow to dry. Repeat steps once daily until the wart is gone.

Directions for Step 1 Apply one or two drops and scrub with a brush Rinse and dry thoroughly

Directions for Step 2 Dab directly onto the wart and allow to dry.

Keep Out of Reach of Children

Warnings

Avoid contact with the eyes. If eye contact does occur, rinse thoroughly with water for 15 minutes. For external use only. Avoid inhaling vapors. Extremely flammable. Keep away from fire or flame. Replace bottle caps tightly and store at room temperature away from heat. Do not use on irritated skin, moles, any areas that is infected or reddened, birthmarks, genital warts, warts with hair growing from them, warts on the face, warts on mucous membranes (such as inside the mouth, nose, anus, genitals, or lips)

Ask A Doctor

Stop and ask a Doctor if discomfort persists. If swallowed get medical help or contact a poison control center right away. Ask a doctor before use if you have diabetes or poor blood circulation.

Package Label

VeruCide 2-step Wart Treatment System Wart Remover Physician Formula Contains Papaya Extract
Questions or comments Call 800-307-8818 Monday through Friday 8:00 am to 5:00 pm (Pacific Time) Please recycle. This package is made from recyclable materials. Proudly made in the USA.